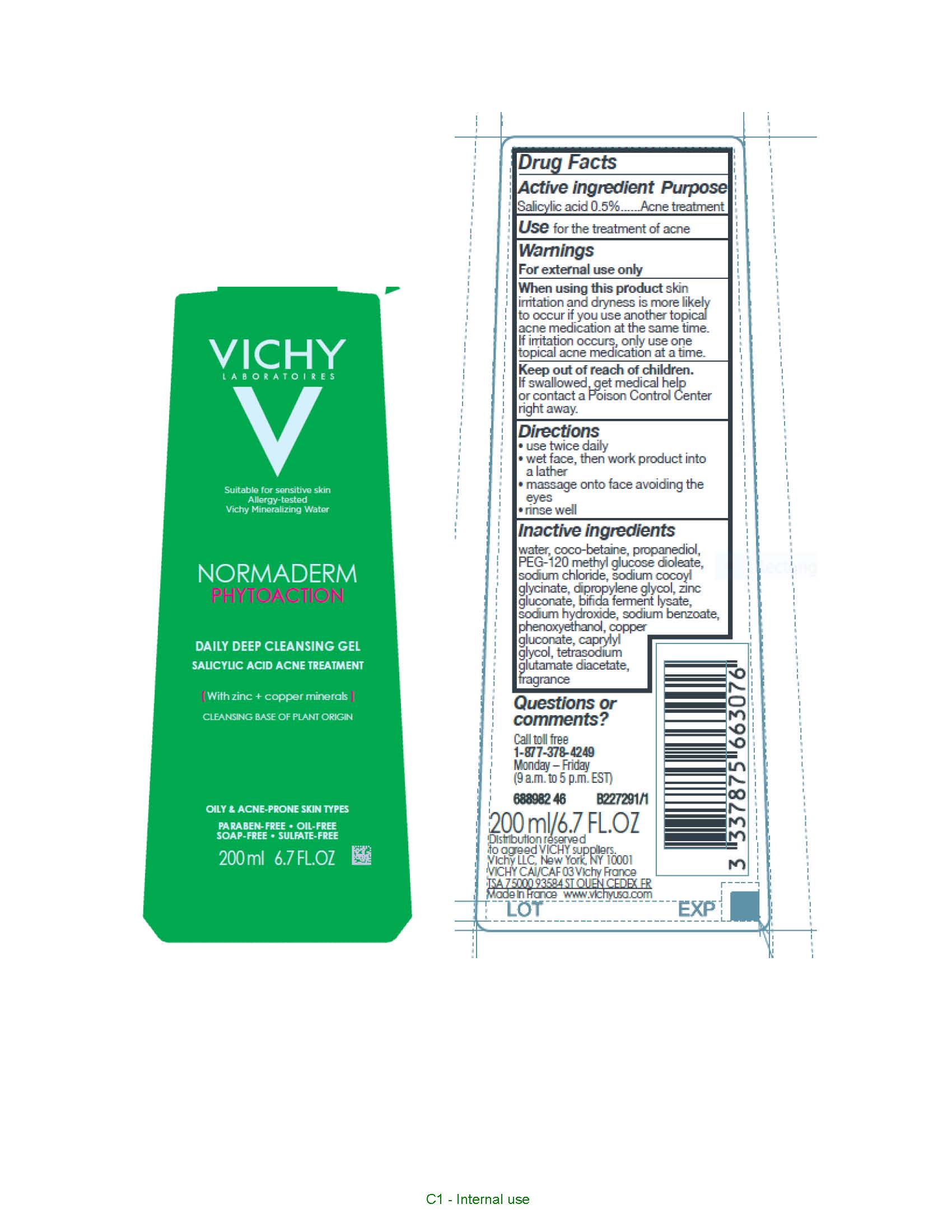 DRUG LABEL: Vichy Laboratoires Normaderm Phytoaction Deep Cleansing
NDC: 69625-306 | Form: GEL
Manufacturer: COSMETIQUE ACTIVE PRODUCTION
Category: otc | Type: HUMAN OTC DRUG LABEL
Date: 20231211

ACTIVE INGREDIENTS: Salicylic Acid 5 mg/1 mL
INACTIVE INGREDIENTS: WATER; COCO-BETAINE; PROPANEDIOL; PEG-120 METHYL GLUCOSE DIOLEATE; SODIUM CHLORIDE; SODIUM COCOYL GLYCINATE; DIPROPYLENE GLYCOL; ZINC GLUCONATE; SODIUM HYDROXIDE; SODIUM BENZOATE; PHENOXYETHANOL; COPPER GLUCONATE; CAPRYLYL GLYCOL; TETRASODIUM GLUTAMATE DIACETATE

Drug Facts

Active ingredient

Salicylic acid...0.5%

Purpose

Acne treatment

Use

for the treatment of acne

Warnings

For external use only

When using this product

kin irritation and dryness is more likely to occur if you use another topical acne medication at the same time. if irritation occurs, only use one topical acne medication at a time.

Keep out of reach of children.

If swallowed, get medical help or contact a Poison Control Center right away.

Directions

- use twice daily
- wet face, then work product into a lather
- massage onto face avoiding the eyes
- rinse well

Inactive ingredients

water, coco-betaine, propanediol, PEG-120 methyl glyucose dioleate, sodium chloride, sodium cocoyl glycinate, dipropylene glycol, zinc gluconate, bifida ferment lysate, sodium hydroxide, sodium benzoate, phenoxyethanol, copper gluconate, caprylyl glycol, tetrasodium glutamate diacetate, fragrance